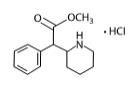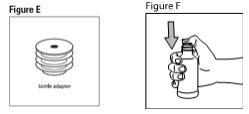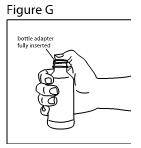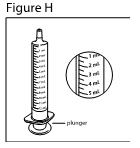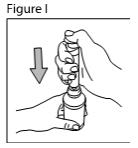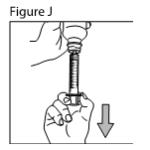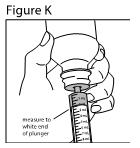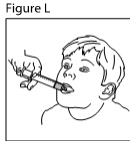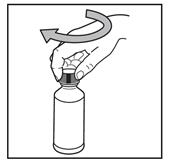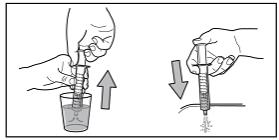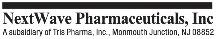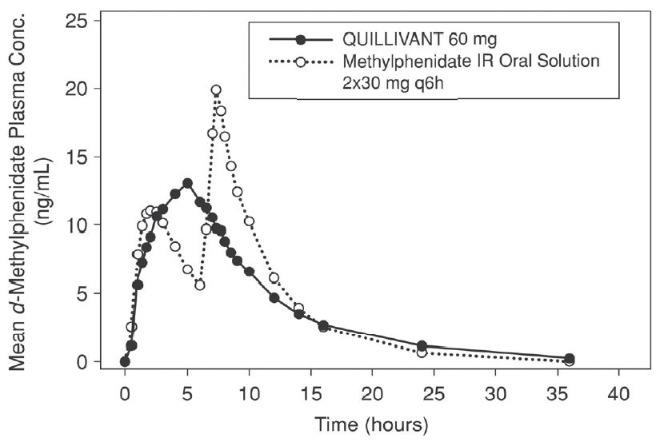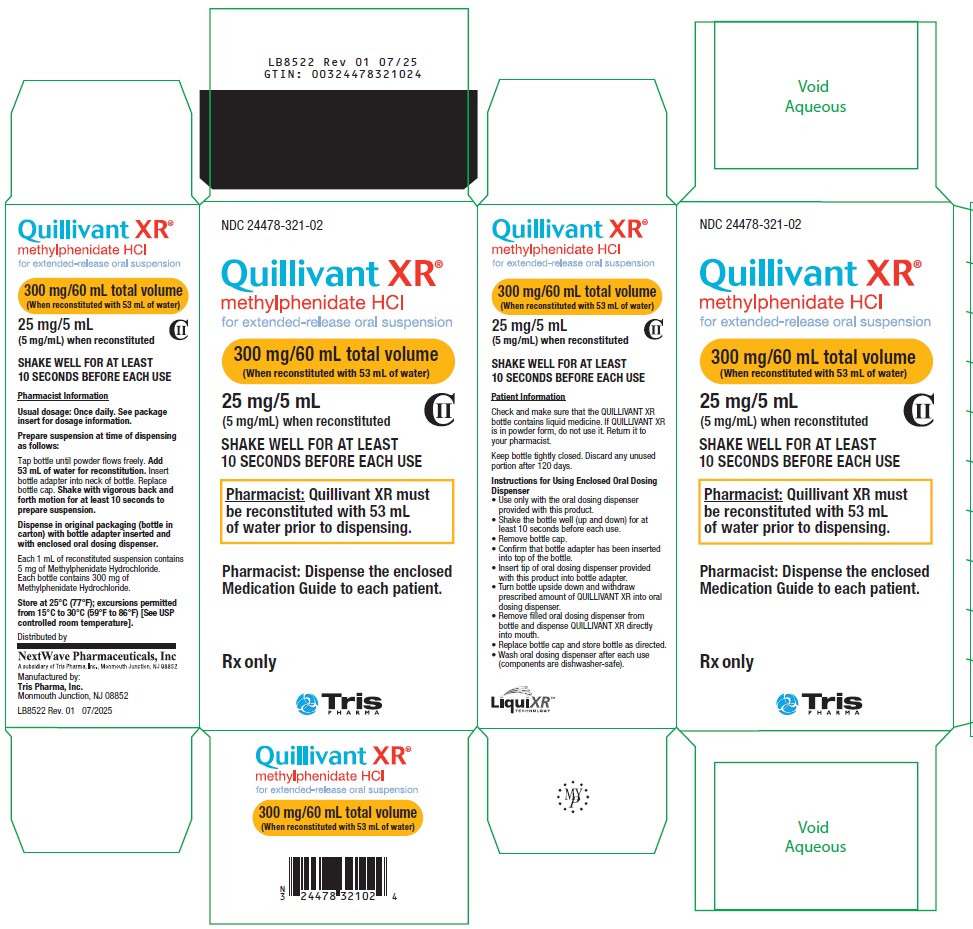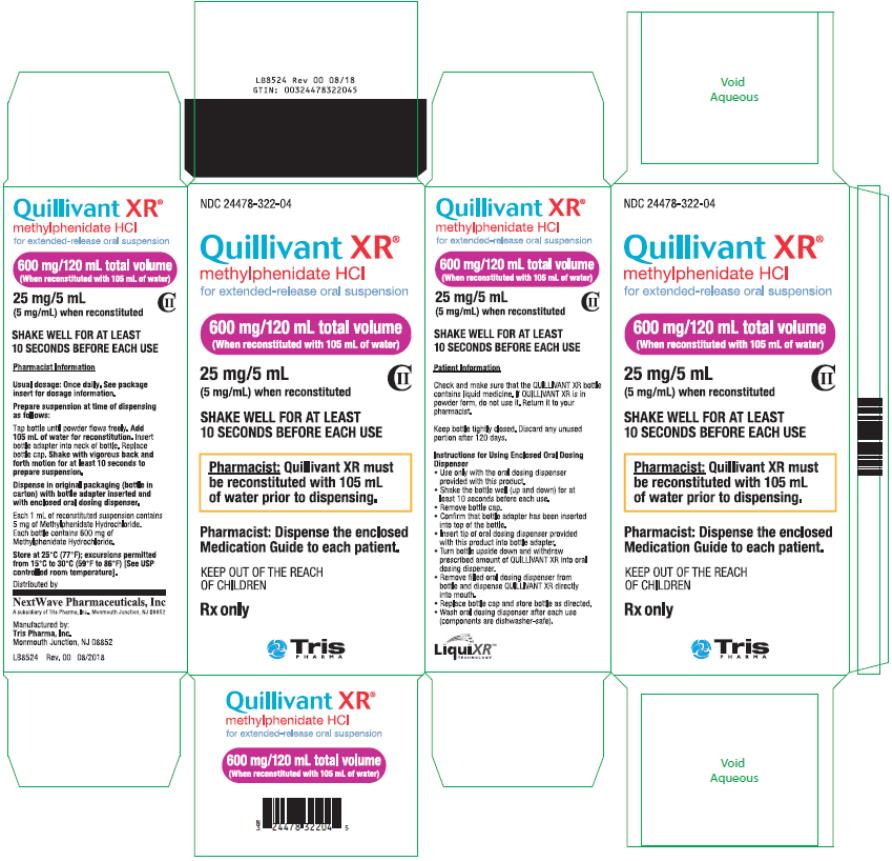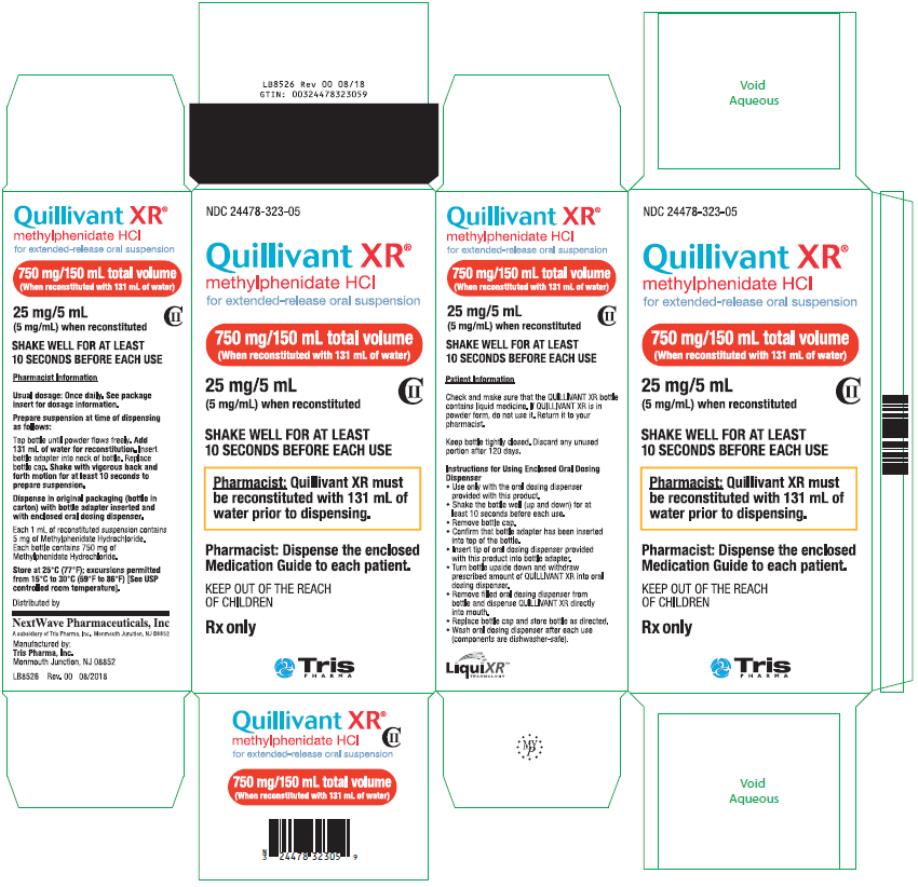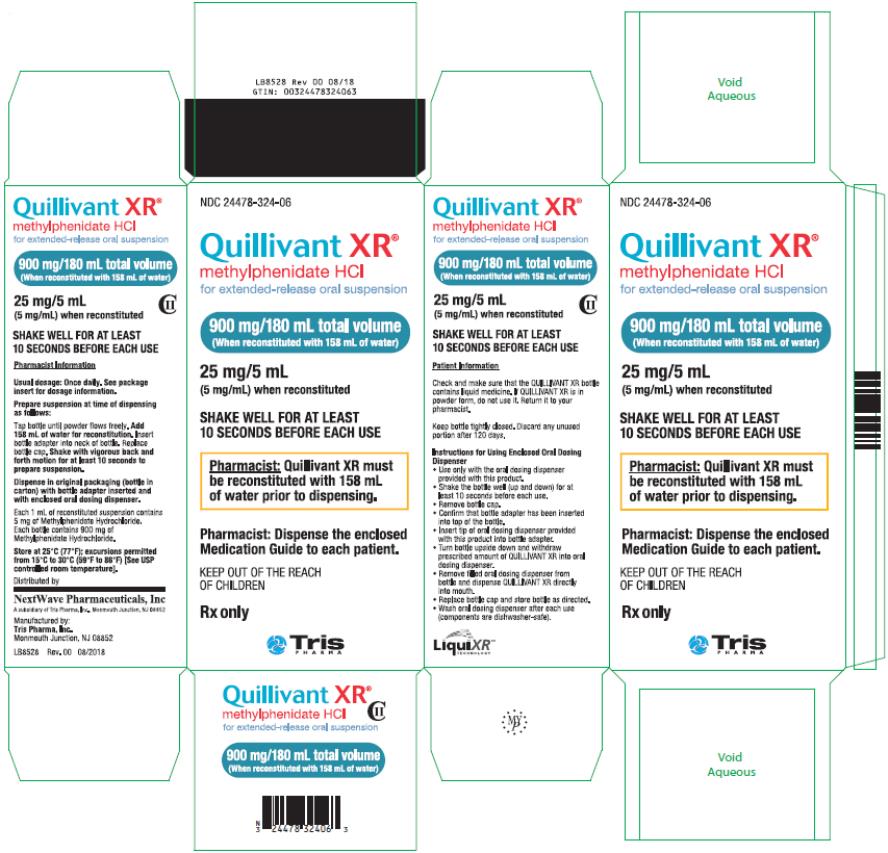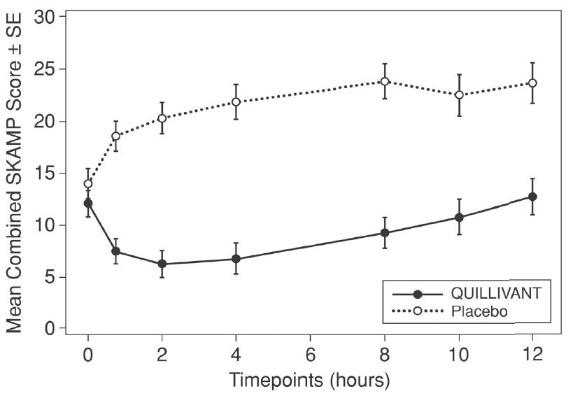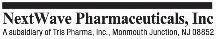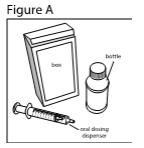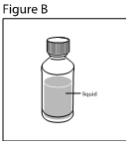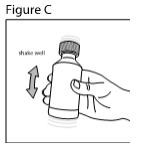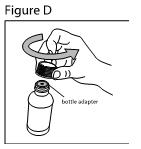 DRUG LABEL: Quillivant
NDC: 24478-321 | Form: SUSPENSION, EXTENDED RELEASE
Manufacturer: NextWave Pharmaceuticals, Inc
Category: prescription | Type: HUMAN PRESCRIPTION DRUG LABEL
Date: 20250930
DEA Schedule: CII

ACTIVE INGREDIENTS: METHYLPHENIDATE HYDROCHLORIDE 300 mg/60 mL
INACTIVE INGREDIENTS: SODIUM POLYSTYRENE SULFONATE; POVIDONE, UNSPECIFIED; TRIACETIN; SUCROSE; ANHYDROUS TRISODIUM CITRATE; ANHYDROUS CITRIC ACID; SODIUM BENZOATE; SUCRALOSE; POLOXAMER 188; STARCH, CORN; XANTHAN GUM; TALC; SILICON DIOXIDE; POLYVINYL ACETATE PHTHALATE

HIGHLIGHTS OF PRESCRIBING INFORMATION

These highlights do not include all the information needed to use QUILLIVANT XR® safely and effectively.
See full prescribing information for QUILLIVANT XR®.
QUILLIVANT XR® (methylphenidate hydrochloride) for extended-release oral suspension, CII
Initial U.S. Approval: 1955

WARNING: ABUSE, MISUSE, AND ADDICTION

See full prescribing information for complete boxed warning.

QUILLIVANT XR has a high potential for abuse and misuse, which can lead to the development of a substance use disorder, including addiction. Misuse and abuse of CNS stimulants, including QUILLIVANT XR, can result in overdose and death (5.1, 9.2, 10):

- Before prescribing QUILLIVANT XR, assess each patient’s risk for abuse, misuse, and addiction.
- Educate patients and their families about these risks, proper storage of the drug, and proper disposal of any unused drug.
- Throughout treatment, reassess each patient’s risk and frequently monitor for signs and symptoms of abuse, misuse, and addiction.

RECENT MAJOR CHANGES

Indications and Usage (1) 09/2025

Warnings and Precautions (5.7) 09/2025

1 INDICATIONS AND USAGE

QUILLIVANT XR is a central nervous system (CNS) stimulant indicated for the treatment of Attention Deficit Hyperactivity Disorder (ADHD). (1)

Limitations of Use

The use of QUILLIVANT XR is not recommended in pediatric patients younger than 6 years of age because they had higher plasma exposure and a higher incidence of adverse reactions (e.g., weight loss) than patients 6 years and older at the same dosage (5.7, 8.4).

2 DOSAGE AND ADMINISTRATION

- Before administering the dose, vigorously shake bottle for at least 10 seconds. (2.2)
- May be taken with or without food. (2.3)
- For patients 6 years and above, recommended starting dose is 20 mg given orally once daily in the morning. Dosage may be increased weekly in increments of 10 mg to 20 mg per day. Daily dosage above 60 mg is not recommended. (2.2)
- Reconstitution instructions for the pharmacist: Tap bottle until powder flows freely. Remove bottle cap, add specified amount of water for reconstitution. Insert bottle adapter into neck of bottle. Replace bottle cap. Shake with vigorous back and forth motion for at least 10 seconds to prepare suspension. (2.6)

3 DOSAGE FORMS AND STRENGTHS

Extended-release oral suspension (after reconstitution with water): 25 mg per 5 mL (5 mg per mL). (3)

4 CONTRAINDICATIONS

- Known hypersensitivity to methylphenidate or product components. (4.1)
- Concurrent treatment with a monoamine oxidase inhibitor (MAOI), or use of an MAOI within the preceding 14 days. (4.2, 7.1)

5 WARNINGS AND PRECAUTIONS

- Risks to Patients with Serious Cardiac Disease: Avoid use in patients with known structural cardiac abnormalities, cardiomyopathy, serious cardiac arrhythmias, coronary artery disease, or other serious cardiac disease. (5.2)
- Increased Blood Pressure and Heart Rate: Monitor blood pressure and pulse. (5.3)
- Psychiatric Adverse Reactions: Prior to initiating QUILLIVANT XR, screen patients for risk factors for developing a manic episode. If new psychotic or manic symptoms occur, consider discontinuing QUILLIVANT XR. (5.4)
- Priapism: If abnormally sustained or frequent and painful erections occur, patients should seek immediate medical attention. (5.5)
- Peripheral Vasculopathy, including Raynaud’s Phenomenon: Careful observation for digital changes is necessary during QUILLIVANT XR treatment. Further clinical evaluation (e.g., rheumatology referral) may be appropriate for patients who develop signs or symptoms of peripheral vasculopathy. (5.6)
- Long-Term Suppression of Growth in Pediatric Patients: Closely monitor growth (height and weight) in pediatric patients. Pediatric patients not growing or gaining height or weight as expected may need to have their treatment interrupted. (5.7)
- Acute Angle Closure Glaucoma: QUILLIVANT XR -treated patients considered at risk for acute angle closure glaucoma (e.g., patients with significant hyperopia) should be evaluated by an ophthalmologist. (5.8)
- Increased Intraocular Pressure (IOP) and Glaucoma: Prescribe QUILLIVANT XR to patients with open-angle glaucoma or abnormally increased IOP only if the benefit of treatment is considered to outweigh the risk. Closely monitor patients with a history of increased IOP or open angle glaucoma. (5.9)
- Motor and Verbal Tics, and Worsening of Tourette’s Syndrome: Before initiating QUILLIVANT XR, assess the family history and clinically evaluate patients for tics or Tourette’s syndrome. Regularly monitor patients for the emergence or worsening of tics or Tourette’s syndrome. Discontinue treatment if clinically appropriate. (5.10)

6 ADVERSE REACTIONS

Based on accumulated data from other methylphenidate products, the most common (≥5% and twice the rate of placebo) adverse reactions are appetite decreased, insomnia, nausea, vomiting, dyspepsia, abdominal pain, weight decreased, anxiety, dizziness, irritability, affect lability, tachycardia, and blood pressure increased. (6.1)

To report SUSPECTED ADVERSE REACTIONS, contact Tris Pharma, Inc. at 732-940-0358 or FDA at 1-800-FDA-1088 or www.fda.gov/medwatch.

7 DRUG INTERACTIONS

- Antihypertensive Drugs: Monitor blood pressure. Adjust dosage of antihypertensive drug as needed. (7)

FULL PRESCRIBING INFORMATION

WARNING: ABUSE, MISUSE, AND ADDICTION

QUILLIVANT XR has a high potential for abuse and misuse, which can lead to the development of a substance use disorder, including addiction. Misuse and abuse of CNS stimulants, including QUILLIVANT XR, can result in overdose and death [see Overdosage (10)], and this risk is increased with higher doses or unapproved methods of administration, such as snorting or injection.

Before prescribing QUILLIVANT XR, assess each patient’s risk for abuse, misuse, and addiction. Educate patients and their families about these risks, proper storage of the drug, and proper disposal of any unused drug. Throughout QUILLIVANT XR treatment, reassess each patient’s risk of abuse, misuse, and addiction and frequently monitor for signs and symptoms of abuse, misuse, and addiction [see Warnings and Precautions (5.1), Drug Abuse and Dependence (9.2)].

1 INDICATIONS AND USAGE

QUILLIVANT XR is indicated for the treatment of Attention Deficit Hyperactivity Disorder (ADHD) [see Clinical Studies (14)].

Limitations of Use

The use of QUILLIVANT XR is not recommended in pediatric patients younger than 6 years of age because they had higher plasma exposure and a higher incidence of adverse reactions (e.g., weight loss) than patients 6 years and older at the same dosage [see Warnings and Precautions (5.7), Use in Specific Populations (8.4)].

2 DOSAGE AND ADMINISTRATION

2.1 Pretreatment Screening

Prior to treating patients with QUILLIVANT XR, assess:

- for the presence of cardiac disease (i.e., perform a careful history, family history of sudden death or ventricular arrhythmia, and physical exam) [see Warnings and Precautions (5.2)].
- the family history and clinically evaluate patients for motor or verbal tics or Tourette’s syndrome before initiating QUILLIVANT XR [see Warnings and Precautions (5.10)].

2.2 Recommended Dosage

Before administering the dose, VIGOROUSLY SHAKE the bottle of QUILLIVANT XR for at least 10 seconds, to ensure that the proper dose is administered.

The recommended starting dose of QUILLIVANT XR for patients 6 years and above is 20 mg once daily in the morning. The dose may be titrated weekly in increments of 10 mg to 20 mg. Daily doses above 60 mg have not been studied and are not recommended. As with any CNS stimulant, during titration of QUILLIVANT XR, the prescribed dose should be adjusted, if necessary, until a well‑tolerated, therapeutic dose is achieved.

Patients should be advised to avoid alcohol while taking QUILLIVANT XR [see Clinical Pharmacology (12.3)].

2.3 Administration Instructions

QUILLIVANT XR should be orally administered once daily in the morning with or without food [see Clinical Pharmacology (12.3)].

2.4 Switching from other Methylphenidate Products

If switching from other methylphenidate products, discontinue that treatment, and titrate with QUILLIVANT XR using the above titration schedule.

Do not substitute for other methylphenidate products on a milligram-per-milligram basis, because of different methylphenidate base compositions and differing pharmacokinetic profiles [see Description (11), Clinical Pharmacology (12.3)].

2.5 Dose Reduction and Discontinuation

If paradoxical aggravation of symptoms or other adverse effects occur, reduce dosage, or, if necessary, discontinue the drug. If improvement is not observed after appropriate dosage adjustment over a one-month period, the drug should be discontinued.

2.6 Reconstitution Instructions for the Pharmacist

QUILLIVANT XR is supplied as a powder for oral suspension which must be reconstituted with water prior to dispensing. Preparation instructions: Tap bottle until powder flows freely. Remove bottle cap, and add specified amount of water to the bottle (see Table 1 below). Fully insert bottle adapter into neck of bottle [see Instructions for Use, Figures F and G]. Replace bottle cap. Shake with vigorous back and forth motion for at least 10 seconds to prepare suspension.

Table 1: Product Reconstitution Instructions
Amount of drug in bottle | Amount of water to add to bottle | Final reconstituted volume (yield)
300 mg | 53 mL | 60 mL
600 mg | 105 mL | 120 mL
750 mg | 131 mL | 150 mL
900 mg | 158 mL | 180 mL

Store reconstituted QUILLIVANT XR at 25ºC (77ºF); excursions permitted from 15º to 30ºC (59º to 86ºF). Dispense in original packaging (bottle in carton) with bottle adapter inserted and with enclosed oral dosing dispenser. QUILLIVANT XR is stable for up to 4 months after reconstitution.

3 DOSAGE FORMS AND STRENGTHS

Extended-release oral suspension (after reconstitution with water): 25 mg per 5 mL (5 mg per mL).

4 CONTRAINDICATIONS

4.1 Hypersensitivity to Methylphenidate or other Components of QUILLIVANT XR

QUILLIVANT XR is contraindicated in patients known to be hypersensitive to methylphenidate, or other components of QUILLIVANT XR. Hypersensitivity reactions such as angioedema and anaphylactic reactions have been reported in patients treated with other methylphenidate products [see Adverse Reactions (6.2)].

4.2 Monoamine Oxidase Inhibitors

QUILLIVANT XR is contraindicated during treatment with monoamine oxidase inhibitors (MAOIs), and also within 14 days following discontinuation of treatment with a monoamine oxidase inhibitor (MAOI), because of the risk of hypertensive crisis [see Drug Interactions (7.1)].

5 WARNINGS AND PRECAUTIONS

5.1 Abuse, Misuse, and Addiction

QUILLIVANT XR has a high potential for abuse and misuse. The use of QUILLIVANT XR exposes individuals to the risks of abuse and misuse, which can lead to the development of a substance use disorder, including addiction. QUILLIVANT XR can be diverted for non-medical use into illicit channels or distribution [see Drug Abuse and Dependence (9.2)]. Misuse and abuse of CNS stimulants, including QUILLIVANT XR, can result in overdose and death [see Overdosage (10)], and this risk is increased with higher doses or unapproved methods of administration, such as snorting or injection.

Before prescribing QUILLIVANT XR, assess each patient’s risk for abuse, misuse, and addiction. Educate patients and their families about these risks and proper disposal of any unused drug. Advise patients to store QUILLIVANT XR in a safe place, preferably locked, and instruct patients to not give QUILLIVANT XR to anyone else. Throughout QUILLIVANT XR treatment, reassess each patient’s risk of abuse, misuse, and addiction and frequently monitor for signs and symptoms of abuse, misuse, and addiction.

5.2 Risks to Patients with Serious Cardiac Disease

Sudden death has occurred in patients with structural cardiac abnormalities or other serious cardiac disease who were treated with CNS stimulants at the recommended ADHD dosage.

Avoid QUILLIVANT XR use in patients with known structural cardiac abnormalities, cardiomyopathy, serious cardiac arrhythmias, coronary artery disease, or other serious cardiac disease.

5.3 Increased Blood Pressure and Heart Rate

CNS stimulants cause an increase in blood pressure (mean increase approximately 2 to 4 mm Hg) and heart rate (mean increase approximately 3 to 6 bpm). Some patients may have larger increases.

Monitor all QUILLIVANT XR-treated patients for hypertension and tachycardia.

5.4 Psychiatric Adverse Reactions

Exacerbation of Pre-Existing Psychosis

CNS stimulants may exacerbate symptoms of behavior disturbance and thought disorder in patients with a pre-existing psychotic disorder.

Induction of a Manic Episode in Patients with Bipolar Disorder

CNS stimulants may induce a manic or mixed episode in patients. Prior to initiating QUILLIVANT XR treatment, screen patients for risk factors for developing a manic episode (e.g., comorbid or history of depressive symptoms or a family history of suicide, bipolar disorder, or depression).

New Psychotic or Manic Symptoms

CNS stimulants, at the recommended dosage, may cause psychotic or manic symptoms (e.g., hallucinations, delusional thinking, or mania) in patients without a prior history of psychotic illness or mania. In a pooled analysis of multiple short-term, placebo-controlled studies of CNS stimulants, psychotic or manic symptoms occurred in approximately 0.1% of CNS stimulant-treated patients, compared to 0% of placebo-treated patients. If such symptoms occur, consider discontinuing QUILLIVANT XR.

5.5 Priapism

Prolonged and painful erections, sometimes requiring surgical intervention, have been reported with methylphenidate use in both adults and pediatric male patients. Although priapism was not reported with methylphenidate initiation, it developed after some time on methylphenidate, often subsequent to an increase in dosage. Priapism also occurred during a methylphenidate withdrawal (drug holidays or during discontinuation).

QUILLIVANT XR-treated patients who develop abnormally sustained or frequent and painful erections should seek immediate medical attention.

5.6 Peripheral Vasculopathy, including Raynaud’s Phenomenon

CNS stimulants, including QUILLIVANT XR, used to treat ADHD are associated with peripheral vasculopathy, including Raynaud’s phenomenon. Signs and symptoms are usually intermittent and mild; however, sequelae have included digital ulceration and/or soft tissue breakdown. Effects of peripheral vasculopathy, including Raynaud’s phenomenon, were observed in post-marketing reports and at the therapeutic dosage of CNS stimulants in all age groups throughout the course of treatment. Signs and symptoms generally improved after dosage reduction or discontinuation of the CNS stimulant.

Careful observation of digital changes is necessary during QUILLIVANT XR treatment. Further clinical evaluation (e.g., rheumatology referral) may be appropriate for QUILLIVANT XR-treated patients who develop signs or symptoms of peripheral vasculopathy.

5.7 Long-Term Suppression of Growth in Pediatric Patients

QUILLIVANT XR is not approved and is not recommended for use in pediatric patients below 6 years of age [see Use in Specific Populations (8.4)].

CNS stimulants have been associated with weight loss and slowing of growth rate in pediatric patients. Careful follow-up of weight and height in pediatric patients ages 7 to 10 years who were randomized to either methylphenidate or nonmedication treatment groups over 14 months, as well as in naturalistic subgroups of newly methylphenidate-treated and nonmedication-treated pediatric patients over 36 months (to the ages of 10 to 13 years), suggests that pediatric patients who received methylphenidate for 7 days per week throughout the year had a temporary slowing in growth rate (on average, a total of about 2 cm less growth in height and 2.7 kg less growth in weight over 3 years), without evidence of growth rebound during this development period.

Closely monitor growth (weight and height) in QUILLIVANT XR-treated pediatric patients. Pediatric patients who are not growing or gaining height or weight as expected may need to have their treatment interrupted.

5.8 Acute Angle Closure Glaucoma

There have been reports of angle closure glaucoma associated with methylphenidate treatment.

Although the mechanism is not clear, QUILLIVANT XR -treated patients considered at risk for acute angle closure glaucoma (e.g., patients with significant hyperopia) should be evaluated by an ophthalmologist.

5.9 Increased Intraocular Pressure and Glaucoma

There have been reports of an elevation of intraocular pressure (IOP) associated with methylphenidate treatment [see Adverse Reactions (6.2)].

Prescribe QUILLIVANT XR to patients with open-angle glaucoma or abnormally increased IOP only if the benefit of treatment is considered to outweigh the risk. Closely monitor QUILLIVANT XR -treated patients with a history of abnormally increased IOP or open angle glaucoma.

5.10 Motor and Verbal Tics, and Worsening of Tourette’s Syndrome

CNS stimulants, including methylphenidate, have been associated with the onset or exacerbation of motor and verbal tics. Worsening of Tourette’s syndrome has also been reported [see Adverse Reactions (6.2)].

Before initiating QUILLIVANT XR, assess the family history and clinically evaluate patients for tics or Tourette’s syndrome. Regularly monitor QUILLIVANT XR -treated patients for the emergence or worsening of tics or Tourette’s syndrome, and discontinue treatment if clinically appropriate.

6 ADVERSE REACTIONS

The following are discussed in more detail in other sections of the labeling:

- Known hypersensitivity to methylphenidate products or other ingredients of QUILLIVANT XR [see Contraindications (4)]
- Hypertensive Crisis When Used Concomitantly with Monoamine Oxidase Inhibitors [see Contraindications (4), Drug Interactions (7.1)]
- Abuse, Misuse, and Addiction [see Boxed Warning, Warnings and Precautions (5.1), Drug Abuse and Dependence (9.2, 9.3)]
- Risks to Patients with Serious Cardiac Disease [see Warnings and Precautions (5.2)]
- Increased Blood Pressure and Heart Rate [see Warnings and Precautions (5.3)]
- Psychiatric Adverse Reactions [see Warnings and Precautions (5.4)]
- Priapism [see Warnings and Precautions (5.5)]
- Peripheral Vasculopathy, including Raynaud’s phenomenon [see Warnings and Precautions (5.6)]
- Long-Term Suppression of Growth in Pediatric Patients [see Warnings and Precautions (5.7)]
- Acute Angle Closure Glaucoma [see Warnings and Precautions (5.8)]
- Increased Intraocular Pressure and Glaucoma [see Warnings and Precautions (5.9)]
- Motor and Verbal Tics, and Worsening of Tourette’s Syndrome [see Warnings and Precautions (5.10)]

6.1 Clinical Trials Experience

Because clinical trials are conducted under widely varying conditions, adverse reaction rates observed in the clinical trials of a drug cannot be directly compared to rates in the clinical trials of another drug and may not reflect the rates observed in clinical practice.

Adverse Reactions in Studies with Other Methylphenidate Products in Children, Adolescents, and Adults with ADHD

Commonly reported (≥2% of the methylphenidate group and at least twice the rate of the placebo group) adverse reactions from placebo-controlled trials of methylphenidate products include: appetite decreased, weight decreased, nausea, abdominal pain, dyspepsia, dry mouth, vomiting, insomnia, anxiety, nervousness, restlessness, affect lability, agitation, irritability, dizziness, vertigo, tremor, blurred vision, blood pressure increased, heart rate increased, tachycardia, palpitations, hyperhidrosis, and pyrexia.

Adverse Reactions in Studies with QUILLIVANT XR in Children and Adolescents with ADHD

There is limited experience with QUILLIVANT XR in controlled trials. Based on this limited experience, the adverse reaction profile of QUILLIVANT XR appears similar to other methylphenidate extended-release products. The most common (≥2% in the QUILLIVANT XR group and greater than placebo) adverse reactions reported in the Phase 3 controlled study conducted in 45 ADHD patients (ages 6 to 12 years) were affect lability, excoriation, initial insomnia, tic, decreased appetite, vomiting, motion sickness, eye pain, and rash.

Table 2: Common Adverse Reactions occurring in ≥2% of subjects on QUILLIVANT XR and greater than placebo during the controlled cross-over phase
Adverse reaction | QUILLIVANT XR N= 45 | Placebo N= 45
Affect lability | 9% | 2%
Excoriation | 4% | 0
Initial Insomnia | 2% | 0
Tic | 2% | 0
Decreased appetite | 2% | 0
Vomiting | 2% | 0
Motion sickness | 2% | 0
Eye pain | 2% | 0
Rash | 2% | 0

6.2 Postmarketing Experience

The following adverse reactions have been identified during post approval use of methylphenidate products. Because these reactions are reported voluntarily from a population of uncertain size, it is not possible to reliably estimate their frequency or establish a causal relationship to drug exposure. These adverse reactions are as follows:

Blood and Lymphatic System Disorders: Pancytopenia, Thrombocytopenia, Thrombocytopenic purpura

Cardiac Disorders: Angina pectoris, Bradycardia, Extrasystole, Supraventricular tachycardia, Ventricular extrasystole

Eye Disorders: Diplopia, Increased intraocular pressure, Mydriasis, Visual impairment

General Disorders: Chest pain, Chest discomfort, Hyperpyrexia

Hepatobiliary Disorders: Severe hepatocellular injury

Immune System Disorders: Hypersensitivity reactions such as Angioedema, Anaphylactic reactions, Auricular swelling, Bullous conditions, Exfoliative conditions, Urticarias, Pruritus NEC, Rashes, Eruptions, and Exanthemas NEC

Investigations: Alkaline phosphatase increased, Bilirubin increased, Hepatic enzyme increased, Platelet count decreased, White blood cell count abnormal

Musculoskeletal, Connective Tissue and Bone Disorders: Arthralgia, Myalgia, Muscle twitching, Rhabdomyolysis

Nervous System Disorders: Convulsion, Grand mal convulsion, Dyskinesia, Serotonin syndrome in combination with serotonergic drugs, Motor and Verbal Tics

Psychiatric Disorders: Disorientation, Hallucination, Hallucination auditory, Hallucination visual, Libido changes, Mania

Urogenital System: Priapism

Skin and Subcutaneous Tissue Disorders: Alopecia, Erythema

Vascular Disorders: Raynaud’s phenomenon

7 DRUG INTERACTIONS

7.1 Clinically Important Drug Interactions

MAOI Inhibitors
Do not administer QUILLIVANT XR concomitantly with monoamine oxidase inhibitors (MAOIs) or within 14 days after discontinuing MAOI treatment. Concomitant use of MAOIs and CNS stimulants can cause hypertensive crisis. Potential outcomes include death, stroke, myocardial infarction, aortic dissection, ophthalmological complications, eclampsia, pulmonary edema, and renal failure.

Antihypertensive Drugs
QUILLIVANT XR may decrease the effectiveness of drugs used to treat hypertension. Monitor blood pressure and adjust the dosage of the hypertensive drug as needed [see Warnings and Precautions (5.3)].
Halogenated Anesthetics
Concomitant use of halogenated anesthetics and QUILLIVANT XR may increase the risk of sudden blood pressure and heart rate increase during surgery. Monitor blood pressure and avoid use of QUILLIVANT XR in patients being treated with anesthetics on the day of surgery.
Risperidone

Combined use of methylphenidate with risperidone when there is a change, whether an increase or decrease, in dosage of either or both medications, may increase the risk of extrapyramidal symptoms (EPS). Monitor for signs of EPS.

8 USE IN SPECIFIC POPULATIONS

8.1 Pregnancy

Pregnancy Exposure Registry

There is a pregnancy exposure registry that monitors pregnancy outcomes in women exposed to ADHD medications during pregnancy. Healthcare providers are encouraged to register patients by calling the National Pregnancy Registry for Psychostimulants at 1-866-961-2388 or visiting online at https://womensmentalhealth.org/clinical-and-research-programs/pregnancyregistry/othermedications/.

Risk Summary

There are limited published studies and small case series that report on the use of methylphenidate in pregnant women; however, the data are insufficient to inform any drug-associated risks. There are clinical considerations [see Clinical Considerations]. No teratogenic effects were observed in embryo-fetal development studies with oral administration of methylphenidate to pregnant rats and rabbits during organogenesis at doses 2 and 11 times, respectively, the maximum recommended human dose (MRHD). However, spina bifida was observed in rabbits at a dose 40 times the MRHD [see Data].

In the U.S. general population, the estimated background risk of major birth defects and miscarriage in clinically recognized pregnancies is 2% to 4% and 15% to 20%, respectively.

Clinical Considerations

Fetal/Neonatal adverse reactions

CNS stimulant medications, such as QUILLIVANT XR, can cause vasoconstriction and thereby decrease placental perfusion. No fetal and/or neonatal adverse reactions have been reported with the use of therapeutic doses of methylphenidate during pregnancy; however, premature delivery and low birth weight infants have been reported in amphetamine-dependent mothers.

Data

Animal Data

In studies conducted in rats and rabbits, methylphenidate was administered orally at doses of up to 75 and 200 mg/kg/day, respectively, during the period of organogenesis. Teratogenic effects (increased incidence of fetal spina bifida) were observed in rabbits at the highest dose, which is approximately 40 times the maximum recommended human dose (MRHD) on a mg/m^2 basis. The no effect level for embryo-fetal development in rabbits was 60 mg/kg/day (11 times the MRHD on a mg/m^2 basis). There was no evidence of specific teratogenic activity in rats, although increased incidences of fetal skeletal variations were seen at the highest dose level (7 times the MRHD on a mg/m^2 basis), which was also maternally toxic. The no effect level for embryo-fetal development in rats was 25 mg/kg/day (2 times the MRHD on a mg/m^2 basis).

8.2 Lactation

Risk Summary

Limited published literature reports that methylphenidate is present in human milk, which resulted in infant doses of 0.16% to 0.7% of the maternal weight-adjusted dosage and a milk/plasma ratio ranging between 1.1 and 2.7. There are no reports of adverse effects on the breastfed infant and no effects on milk production. Long-term neurodevelopmental effects on infants from CNS stimulant exposure are unknown. The developmental and health benefits of breastfeeding should be considered along with the mother’s clinical need for QUILLIVANT XR and any potential adverse effects on the breastfed infant from QUILLIVANT XR or from the underlying maternal condition.

Clinical Considerations

Monitor breastfeeding infants for adverse reactions, such as agitation, insomnia, anorexia, and reduced weight gain.

8.4 Pediatric Use

The safety and effectiveness of QUILLIVANT XR have not been established in pediatric patients below the age of 6 years.

In studies evaluating extended-release methylphenidate products, patients 4 to <6 years of age had higher systemic methylphenidate exposures than those observed in older pediatric patients at the same dosage. Pediatric patients 4 to <6 years of age also had a higher incidence of adverse reactions, including weight loss.

The safety and effectiveness of QUILLIVANT XR have been established in pediatric patients ages 6 to 17 years. Use of QUILLIVANT XR in pediatric patients 6 to 12 years of age is supported by one adequate and well-controlled study [see Clinical Studies (14)]. Use in 12 to 17 year old’s is supported by the adequate and well-controlled studies of QUILLIVANT XR in younger pediatric patients and additional pharmacokinetic data in adolescents, along with safety information from other methylphenidate‑containing products.

Long Term Suppression of Growth

Growth should be monitored during treatment with CNS stimulants, including QUILLIVANT XR. Children who are not growing or gaining weight as expected may need to have their treatment interrupted [see Warnings and Precautions (5.7)].

Juvenile Animal Data

Rats treated with methylphenidate early in the postnatal period through sexual maturation demonstrated a decrease in spontaneous locomotor activity in adulthood. A deficit in acquisition of a specific learning task was observed in females only. The doses at which these findings were observed are at least 6 times the maximum recommended human dose (MRHD) on a mg/m^2 basis.

In the study conducted in young rats, methylphenidate was administered orally at doses of up to 100 mg/kg/day for 9 weeks, starting early in the postnatal period (postnatal day 7) and continuing through sexual maturity (postnatal week 10). When these animals were tested as adults (postnatal weeks 13 to 14), decreased spontaneous locomotor activity was observed in males and females previously treated with 50 mg/kg/day (approximately 6 times the maximum recommended human dose [MRHD] on a mg/m^2 basis) or greater, and a deficit in the acquisition of a specific learning task was observed in females exposed to the highest dose (12 times the MRHD on a mg/m^2 basis). The no effect level for juvenile neurobehavioral development in rats was 5 mg/kg/day (half the MRHD on a mg/m^2 basis). The clinical significance of the long-term behavioral effects observed in rats is unknown.

8.5 Geriatric Use

QUILLIVANT XR has not been studied in patients over the age of 65 years.

9 DRUG ABUSE AND DEPENDENCE

9.1 Controlled Substance

QUILLIVANT XR contains methylphenidate, a Schedule II controlled substance.

9.2 Abuse

QUILLIVANT XR has a high potential for abuse and misuse which can lead to the development of a substance use disorder, including addiction [see Warnings and Precautions (5.1)]. QUILLIVANT XR can be diverted for non-medical use into illicit channels or distribution.

Abuse is the intentional non-therapeutic use of a drug, even once, to achieve a desired psychological or physiological effect. Misuse is the intentional use, for therapeutic purposes, of a drug by an individual in a way other than prescribed by a health care provider or for whom it was not prescribed. Drug addiction is a cluster of behavioral, cognitive, and physiological phenomena that may include a strong desire to take the drug, difficulties in controlling drug use (e.g., continuing drug use despite harmful consequences, giving a higher priority to drug use than other activities and obligations), and possible tolerance or physical dependence.

Misuse and abuse of methylphenidate may cause increased heart rate, respiratory rate, or blood pressure; sweating; dilated pupils; hyperactivity; restlessness; insomnia; decreased appetite; loss of coordination; tremors; flushed skin; vomiting; and/or abdominal pain. Anxiety, psychosis, hostility, aggression, and suicidal or homicidal ideation have also been observed with CNS stimulants abuse and/or misuse. Misuse and abuse of CNS stimulants, including QUILLIVANT XR, can result in overdose and death [see Overdosage (10)], and this risk is increased with higher doses or unapproved methods of administration, such as snorting or injection.

9.3 Dependence

Physical Dependence

QUILLIVANT XR may produce physical dependence. Physical dependence is a state that develops as a result of physiological adaptation in response to repeated drug use, manifested by withdrawal signs and symptoms after abrupt discontinuation or a significant dose reduction of a drug.

Withdrawal signs and symptoms after abrupt discontinuation or dose reduction following prolonged use of CNS stimulants including QUILLIVANT XR include dysphoric mood; depression; fatigue; vivid, unpleasant dreams; insomnia or hypersomnia; increased appetite; and psychomotor retardation or agitation.

Tolerance

QUILLIVANT XR may produce tolerance. Tolerance is a physiological state characterized by a reduced response to a drug after repeated administration (i.e., a higher dose of a drug is required to produce the same effect that was once obtained at a lower dose).

10 OVERDOSAGE

Clinical Effects of Overdose

Overdose of CNS stimulants is characterized by the following sympathomimetic effects:

- Cardiovascular effects including tachyarrhythmias, and hypertension or hypotension. Vasospasm, myocardial infarction, or aortic dissection may precipitate sudden cardiac death. Takotsubo cardiomyopathy may develop.
- CNS effects including psychomotor agitation, confusion, and hallucinations. Serotonin syndrome, seizures, cerebral vascular accidents, and coma may occur.
- Life-threatening hyperthermia (temperatures greater than 104°F) and rhabdomyolysis may develop.

Overdose Management

Consider the possibility of multiple drug ingestion. The pharmacokinetic profile of QUILLIVANT XR should be considered when treating patients with overdose. Because methylphenidate has a large volume of distribution and is rapidly metabolized, dialysis is not useful. Consider contacting the Poison Help line (1-800-222-1222) or a medical toxicologist for additional overdose management recommendations.

11 DESCRIPTION

QUILLIVANT XR is a powder that, after reconstitution with water, forms an extended-release oral suspension formulation of methylphenidate intended for once daily oral administration. QUILLIVANT XR contains approximately 20% immediate-release and 80% extended-release methylphenidate. After reconstitution, QUILLIVANT XR is available in a 25 mg per 5 mL (5 mg per mL) extended-release oral suspension.

Methylphenidate HCl is a central nervous system (CNS) stimulant. The chemical name is methyl α-phenyl-2-piperidineacetate hydrochloride, and its structural formula is shown in Figure 1.

Figure 1: Methylphenidate HCl structure

C14H19NO2•HCI Mol. Wt. 269.77

Methylphenidate HCl is a white, odorless crystalline powder. Its solutions are acid to litmus. It is freely soluble in water and in methanol, soluble in alcohol, and slightly soluble in chloroform and in acetone.

QUILLIVANT XR also contains the following inactive ingredients: sodium polystyrene sulfonate, povidone, triacetin, polyvinyl acetate, sucrose, anhydrous trisodium citrate, anhydrous citric acid, sodium benzoate, sucralose, poloxamer 188, corn starch, xanthan gum, talc, banana flavor, and silicon dioxide.

12 CLINICAL PHARMACOLOGY

12.1 Mechanism of Action

Methylphenidate HCl is a central nervous system (CNS) stimulant.

12.2 Pharmacodynamics

Methylphenidate is a racemic mixture comprised of the d- and l-isomers. The d-isomer is more pharmacologically active than the l‑isomer. The mode of therapeutic action in ADHD is not known. Methylphenidate blocks the reuptake of norepinephrine and dopamine into the presynaptic neuron and increases the release of these monoamines into the extraneuronal space.

12.3 Pharmacokinetics

Absorption

Following a single, 60 mg oral dose of QUILLIVANT XR in 28 healthy adult subjects in a crossover study under fasting conditions, d-methylphenidate (d-MPH) mean (± SD) peak plasma concentrations of 13.6 (± 5.8) ng/mL occurred at a median time of 5 hours after dosing (Figure 2). The relative bioavailability of QUILLIVANT XR compared to Methylphenidate IR oral solution (2x30 mg, q6h) is 95%.

Figure 2: Mean d-Methylphenidate Plasma Concentration-Time Profiles

The single dose pharmacokinetics of d-MPH under fed conditions are summarized (Table 3) from studies in children and adolescents with ADHD, and healthy adults following an oral dose of 60 mg QUILLIVANT XR.

Table 3: d-MPH PK Parameters (mean ±SD) after 60 mg oral dosing of QUILLIVANT XR*
PK Parameter | Children† (n=3) | Adolescent† (n=4) | Adult (n=27)
Tmax (hr)‡ | 4.05 (3.98-6.0) | 2.0 (1.98-4.0) | 4.0 (1.3-7.3)
T1/2 (hr) | 5.2±0.1 | 5.0±0.2 | 5.2±1.0
Cmax (ng/mL) | 34.4±14.0 | 21.1±5.9 | 17.0±7.7
AUCinf (hr*ng/mL) | 378±175 | 178±54.2 | 163.2±80.3
Cl (L/hr/kg) | 4.27±0.70 | 5.06±1.42 | 5.66±2.15

* Breakfast was given 30 min prior to drug administration† total MPH measured in children (9 to 12 years old) and adolescents (13 to 15 years old), l-MPH <2% of d-MPH in circulation‡ data presented as median (range)

Food Effects

In a study in adult volunteers to investigate the effects of a high-fat meal on the bioavailability of QUILLIVANT XR at a dose of 60 mg, the presence of food reduced the time to peak concentration by approximately 1 hour (fed: 4 hours vs. fasted: 5 hours). Overall, a high-fat meal increased the average Cmax of QUILLIVANT XR by about 28% and the AUC by about 19%. These changes are not considered clinically significant.

Elimination

Following a single 60 mg oral dose of QUILLIVANT XR in 28 healthy adult subjects under fasting conditions, the mean plasma terminal elimination half-life of d-methylphenidate was 5.6 (± 0.8) hours.

Metabolism

In humans, methylphenidate is metabolized primarily via deesterification to alpha-phenyl-piperidine acetic acid (PPAA). The metabolite has little or no pharmacologic activity.

Excretion

After oral dosing of radiolabeled methylphenidate in humans, about 90% of the radioactivity was recovered in urine. The main urinary metabolite was PPAA, accounting for approximately 80% of the dose.

Alcohol Effect

An in vitro study was conducted to explore the effect of alcohol on the release characteristics of methylphenidate from QUILLIVANT XR Oral Suspension. At alcohol concentrations of 5% and 10%, there was no effect of alcohol on the release characteristics of methylphenidate. At 20% alcohol concentration, there was on average a 20% increase in drug exposure [see Dosage and Administration (2.2)].

Specific Populations

Sex

There is insufficient experience with the use of QUILLIVANT XR to detect gender variations in pharmacokinetics.

Race

There is insufficient experience with the use of QUILLIVANT XR to detect ethnic variations in pharmacokinetics.

Age

The pharmacokinetics of methylphenidate after QUILLIVANT XR administration were studied in pediatric patients with ADHD between 9 and 15 years of age. After a single oral dose of 60 mg QUILLIVANT XR, plasma concentrations of methylphenidate in children (9 to 12 years old; n=3) were approximately twice the concentrations observed in adults. The plasma concentrations in adolescent patients (13 to 15 years old; n=4) were similar to those in adults.

Renal Impairment

There is no experience with the use of QUILLIVANT XR in patients with renal insufficiency. After oral administration of radiolabeled methylphenidate in humans, methylphenidate was extensively metabolized and approximately 80% of the radioactivity was excreted in the urine in the form of PPAA. Since renal clearance is not an important route of methylphenidate clearance, renal insufficiency is expected to have little effect on the pharmacokinetics of QUILLIVANT XR.

Hepatic Impairment

There is no experience with the use of QUILLIVANT XR in patients with hepatic insufficiency.

13 NONCLINICAL TOXICOLOGY

13.1 Carcinogenesis, Mutagenesis, Impairment of Fertility

Carcinogenesis

In a lifetime carcinogenicity study carried out in B6C3F1 mice, methylphenidate caused an increase in hepatocellular adenomas and, in males only, an increase in hepatoblastomas, at a daily dose of approximately 60 mg/kg/day. This dose is approximately 4 times the maximum recommended human dose on a mg/m^2 basis. Hepatoblastoma is a relatively rare rodent malignant tumor type. There was no increase in total malignant hepatic tumors. The mouse strain used is sensitive to the development of hepatic tumors, and the significance of these results to humans is unknown.

Methylphenidate did not cause any increase in tumors in a lifetime carcinogenicity study carried out in F344 rats; the highest dose used was approximately 45 mg/kg/day, which is approximately 5 times the maximum recommended human dose on a mg/m^2 basis.

Mutagenesis

Methylphenidate was not mutagenic in the in vitro Ames reverse mutation assay or in the in vitro mouse lymphoma cell forward mutation assay. Sister chromatid exchanges and chromosome aberrations were increased, indicative of a weak clastogenic response, in an in vitro assay in cultured Chinese Hamster Ovary (CHO) cells. Methylphenidate was negative in an in vivo mouse bone marrow micronucleus assay.

Impairment of Fertility

Methylphenidate did not impair fertility in male or female mice that were fed diets containing the drug in an 18-week Continuous Breeding study. The study was conducted at doses of up to 160 mg/kg/day, approximately 8-fold the maximum recommended human dose on a mg/m^2 basis.

14 CLINICAL STUDIES

The efficacy of QUILLIVANT XR was evaluated in a laboratory classroom study conducted in 45 pediatric patients (ages 6 to 12 years) with ADHD. Patients in the trial met Diagnostic and Statistical Manual of Mental Diseases, 4th edition (DSM-IV®) criteria for ADHD. The study began with an open-label dose optimization period (4 to 6 weeks) with an initial QUILLIVANT XR dose of 20 mg once daily in the morning. The dose could be titrated weekly in increments of 10 or 20 mg until a therapeutic dose or the maximum dose of 60 mg/day was reached. At the end of the dose optimization period, approximately 5% of subjects were receiving 20 mg/day; 39%, 30 mg/day; 31%, 40 mg/day; 10%, 50 mg/day; and 15%, 60 mg/day. Subjects then entered a 2-week randomized, double-blind, crossover treatment with the individually optimized dose of QUILLIVANT XR or placebo. At the end of each week, school teachers and raters evaluated the attention and behavior of the subjects in a laboratory classroom using the Swanson, Kotkin, Agler, M-Flynn, and Pelham (SKAMP) rating scale. The primary efficacy endpoint was the SKAMP-Combined score at 4 hours post-dosing. The key secondary efficacy endpoints were the SKAMP-Combined scores at 0.75, 2, 8, 10, and 12 hours post-dosing.

Results from the first double-blind, placebo-controlled week of the study are summarized in Figure 3. SKAMP-Combined scores were statistically significantly lower (improved) at all time points (0.75, 2, 4, 8, 10, 12 hours) post-dosing with QUILLIVANT XR compared to placebo.

Figure 3: Absolute SKAMP-Combined Score after treatment with QUILLIVANT XR or Placebo during Period 1.

16 HOW SUPPLIED/STORAGE AND HANDLING

16.1 How Supplied

QUILLIVANT XR is supplied as powder that, after reconstitution with water, forms an extended-release oral suspension. The product is supplied in a carton. Each carton also contains one bottle, one oral dosing dispenser, and one bottle adapter.

The product must be reconstituted only by the pharmacist and not by the patient or caregiver. After reconstitution, the product is a light beige to tan viscous suspension containing 25 mg per 5 mL (5 mg per mL) of methylphenidate hydrochloride.

Bottles of 300 mg powder (to prepare 60 mL suspension) NDC 24478-321-02

Bottles of 600 mg powder (to prepare 120 mL suspension) NDC 24478-322-04

Bottles of 750 mg powder (to prepare 150 mL suspension) NDC 24478-323-05

Bottles of 900 mg powder (to prepare 180 mL suspension) NDC 24478-324-06

16.2 Storage and Handling

Store at 25ºC (77ºF); excursions permitted from 15ºC to 30ºC (59ºF to 86ºF). [See USP Controlled Room Temperature.]

Dispense in original container.

17 PATIENT COUNSELING INFORMATION

Advise patients to read the FDA-approved patient labeling (Medication Guide and Instructions for Use).

Abuse, Misuse, and Addiction

Educate patients and their families about the risks of abuse, misuse, and addiction of QUILLIVANT XR, which can lead to overdose and death, and proper disposal of any unused drug [see Warnings and Precautions (5.1), Drug Abuse and Dependence (9.2), Overdosage (10)]. Advise patients to store QUILLIVANT XR in a safe place, preferably locked, and instruct patients to not give QUILLIVANT XR to anyone else.

Instructions for Using the Enclosed Oral Dosing Dispenser

Provide the following instructions on administration to the patient or caregiver:

- The pharmacist should provide this medicine in its original packaging (bottle within carton) with the bottle adapter fully inserted and the accompanying oral dosing dispenser. Use only with the oral dosing dispenser provided with this product.
- Check and make sure that the QUILLIVANT XR bottle contains liquid medicine. If QUILLIVANT XR is in powder form, do not use it. Return it to your pharmacist.
- VIGOROUSLY SHAKE the bottle of QUILLIVANT XR for at least 10 seconds before each dose, to ensure that the proper dose is administered.
- Remove the bottle cap. Confirm that the bottle adapter has been inserted into top of the bottle.
- Insert the tip of the oral dosing dispenser provided with this product into the bottle adapter.
- Turn bottle upside down and withdraw prescribed amount of QUILLIVANT XR into the oral dosing dispenser.
- Remove filled oral dosing dispenser from bottle and dispense QUILLIVANT XR directly into mouth.
- Replace bottle cap and store bottle as directed.
- Wash oral dosing dispenser after each use (components are dishwasher-safe).

Risks to Patients with Serious Cardiac Disease

Advise patients that there are potential risks to patients with serious cardiac disease, including sudden death with QUILLIVANT XR use. Instruct patients to contact a health care provider immediately if they develop symptoms such as exertional chest pain, unexplained syncope, or other symptoms suggestive of cardiac disease [see Warnings and Precautions (5.2)].

Increased Blood Pressure and Heart Rate

Advise patients that QUILLIVANT XR can elevate blood pressure and heart rate [see Warnings and Precautions (5.3)].

Psychiatric Adverse Reactions

Advise patients that QUILLIVANT XR, at recommended doses, can cause psychotic or manic symptoms, even in patients without a prior history of psychotic symptoms or mania [see Warnings and Precautions (5.4)].

Priapism

Advise patients, caregivers, and family members of the possibility of painful or prolonged penile erections (priapism). Instruct the patient to seek immediate medical attention in the event of priapism [see Warnings and Precautions (5.5)].

Circulation Problems in Fingers and Toes [Peripheral Vasculopathy, including Raynaud’s Phenomenon]

- Instruct patients beginning treatment with QUILLIVANT XR about the risk of peripheral vasculopathy, including Raynaud’s phenomenon, and associated signs and symptoms: fingers or toes may feel numb, cool, painful, and/or may change color from pale, to blue, to red.
- Instruct patients to report to their physician any new numbness, pain, skin color change, or sensitivity to temperature in fingers or toes.
- Instruct patients to call their physician immediately with any signs of unexplained wounds appearing on fingers or toes while taking QUILLIVANT XR.
- Further clinical evaluation (e.g., rheumatology referral) may be appropriate for certain patients [see Warnings and Precautions (5.6)].

Long-Term Suppression of Growth in Pediatric Patients

Advise patients, families, and caregivers that QUILLIVANT XR can cause slowing of growth and weight loss [see Warnings and Precautions (5.7)].

Increased Intraocular Pressure (IOP) and Glaucoma

Advise patients that IOP and glaucoma may occur during treatment with QUILLIVANT XR [see Warnings and Precautions (5.9)].

Motor and Verbal Tics, and Worsening of Tourette’s Syndrome

Advise patients that motor and verbal tics and worsening of Tourette’s Syndrome may occur during treatment with QUILLIVANT XR. Instruct patients to notify their healthcare provider if emergence of new tics or worsening of tics or Tourette’s syndrome occurs [see Warnings and Precautions (5.10)].

Pregnancy Registry

Advise patients that there is a pregnancy exposure registry that monitors pregnancy outcomes in women exposed to QUILLIVANT XR during pregnancy [see Use in Specific Populations (8.1)].

Alcohol Effect

Patients should be advised to avoid alcohol while taking QUILLIVANT XR Oral Suspension. Consumption of alcohol while taking QUILLIVANT XR may result in a more rapid release of the dose of methylphenidate [see Clinical Pharmacology (12.3)].

This product’s label may have been updated. For current full prescribing information, please visit www.trispharma.com.

Distributed by:

Manufactured by:
Tris Pharma, Inc.
Monmouth Junction, NJ 08852

LB8529 Rev. 03

Medication Guide

QUILLIVANT XR® (\kwil-ə-vant\)
(methylphenidate hydrochloride) for extended-release oral suspension CII

What is the most important information I should know about QUILLIVANT XR?

QUILLIVANT XR may cause serious side effects, including:

- Abuse, misuse, and addiction. QUILLIVANT XR has a high chance for abuse and misuse and may lead to substance use problems, including addiction. Misuse and abuse of QUILLIVANT XR, other methylphenidate containing medicines, and amphetamine containing medicines, can lead to overdose and death. The risk of overdose and death is increased with higher doses of QUILLIVANT XR or when it is used in ways that are not approved, such as snorting or injection.

- Your healthcare provider should check you or your child’s risk for abuse, misuse, and addiction before starting treatment with QUILLIVANT XR and will monitor you or your child during treatment.

- QUILLIVANT XR may lead to physical dependence after prolonged use, even if taken as directed by your healthcare provider.

- Do not give QUILLIVANT XR to anyone else. See “What is QUILLIVANT XR?” for more information.

- Keep QUILLIVANT XR in a safe place and properly dispose of any unused medicine. See “How should I store QUILLIVANT XR?” for more information.

- Tell your healthcare provider if you or your child have ever abused or been dependent on alcohol, prescription medicines, or street drugs.

- Risks for people with serious heart disease. Sudden death has happened in people who have heart defects or other serious heart disease.
  - Your healthcare provider should check you or your child carefully for heart problems before starting treatment with QUILLIVANT XR.

Tell your health care provider if you or your child have any heart problems, heart disease, or heart defects.

Call your healthcare provider or go to the nearest hospital emergency room right away if you or your child has any signs of heart problems such as chest pain, shortness of breath, or fainting while taking QUILLIVANT XR.

- Increased blood pressure and heart rate.
  Your health care provider should check your or your child’s blood pressure and heart rate regularly during treatment with QUILLIVANT XR.
- Mental (Psychiatric) problems:

- new or worse behavior and thought problems
- new or worse bipolar illness
- new psychotic symptoms (such as hearing voices, believing things that are not true, are suspicious) or new manic symptoms

Tell your health care provider about any mental problems you or your child have, or about a family history of suicide, bipolar illness, or depression.

Call your health care provider right away if you or your child have any new or worsening mental symptoms or problems while taking QUILLIVANT XR, especially seeing or hearing things that are not real, believing things that are not real, or are suspicious.

What is QUILLIVANT XR?

QUILLIVANT XR is a central nervous system stimulant prescription medicine. QUILLIVANT XR is a liquid medicine that you take by mouth.

It is used for the treatment of Attention Deficit Hyperactivity Disorder (ADHD). QUILLIVANT XR may help increase attention and decrease impulsiveness and hyperactivity in people with ADHD.

QUILLIVANT XR is not recommended for use in children under 6 years of age with ADHD.

QUILLIVANT XR is a federally controlled substance (CII) because it contains methylphenidate that can be a target for people who abuse prescription medicines or street drugs. Keep QUILLIVANT XR in a safe place to protect it from theft. Never give your QUILLIVANT XR to anyone else, because it may cause death or harm them. Selling or giving away QUILLIVANT XR may harm others and is against the law.

Do not take QUILLIVANT XR if you or your child:

- are allergic to methylphenidate hydrochloride, or any of the ingredients in QUILLIVANT XR. See the end of this Medication Guide for a complete list of ingredients in QUILLIVANT XR.
- are taking or have taken within the past 14 days a type of anti-depression medicine called a monoamine oxidase inhibitor (MAOI).

QUILLIVANT XR may not be right for you or your child. Before starting QUILLIVANT XR tell your or your child’s health care provider about all health conditions (or a family history of) including:

- heart problems, heart disease, heart defects, or high blood pressure
- mental problems including psychosis, mania, bipolar illness, or depression
- circulation problems in fingers and toes
- have eye problems, including increased pressure in your eye, glaucoma, or problems with your close-up vision (farsightedness)
- have or had repeated movements or sounds (tics) or Tourette’s syndrome, or have a family history of tics or Tourette’s syndrome
- if you are pregnant or plan to become pregnant. It is not known if QUILLIVANT XR will harm your unborn baby. Talk to your health care provider if you are pregnant or plan to become pregnant.
  - There is a pregnancy registry for females who are exposed to ADHD medications during pregnancy. The purpose of the registry is to collect information about the health of females exposed to QUILLIVANT XR and their baby. If you or your child becomes pregnant during treatment with QUILLIVANT XR, talk to your healthcare provider about registering with the National Pregnancy Registry for Psychostimulants at 1-866-961-2388 or visit https://womensmentalhealth.org/clinical-and-research-programs/pregnancyregistry/othermedications/.
- if you are breastfeeding or plan to breast feed. QUILLIVANT XR passes into your breast milk. You and your healthcare provider should decide if you will take QUILLIVANT XR or breast feed.

Tell your health care provider about all of the medicines that you or your child take including prescription and nonprescription medicines, vitamins, and herbal supplements. QUILLIVANT XR and some medicines may interact with each other and cause serious side effects. Sometimes the doses of other medicines will need to be adjusted while taking QUILLIVANT XR.

Your health care provider will decide whether QUILLIVANT XR can be taken with other medicines.

Especially tell your health care provider if you or your child takes:

- anti-depression medicines including MAOIs

Know the medicines that you or your child takes. Keep a list of your medicines with you to show your health care provider and pharmacist. Do not start any new medicine while taking QUILLIVANT XR without talking to your health care provider first.

How should QUILLIVANT XR be taken?

- Read the step-by-step instructions for using QUILLIVANT XR extended-release suspension at the end of this Medication Guide.

- Take QUILLIVANT XR exactly as prescribed. Your health care provider may adjust the dose, if needed, until it is right for you or your child. During dose adjustment, you or your child may still have ADHD symptoms.
- QUILLIVANT XR should be used with the oral dosing dispenser provided with the product. If the oral dosing dispenser is missing or not provided, please contact your pharmacist for a replacement.
- Check and make sure that the QUILLIVANT XR bottle contains liquid medicine. If QUILLIVANT XR is in powder form, do not use it. Return it to your pharmacist.
- Check and make sure that the bottle adapter was fully inserted into the bottle by the pharmacist. If the bottle adapter is not fully inserted, insert the adapter into the bottle.
- Take QUILLIVANT XR 1 time each day in the morning. QUILLIVANT XR is an extended-release suspension. It releases medicine into your body throughout the day.
- QUILLIVANT XR can be taken with or without food. Taking QUILLIVANT XR with food may shorten the time it takes for the medicine to start working.
- Your health care provider may do regular checks of the blood, heart, and blood pressure while taking QUILLIVANT XR.
- Children should have their height and weight checked often while taking QUILLIVANT XR. QUILLIVANT XR treatment may be stopped if a problem is found during these check-ups.
- If a dose is missed, you or your child should talk to your health care provider about dosing.

If you or your child take too much QUILLIVANT XR, call your healthcare provider or Poison Help line at 1-800-222-1222 or go to the nearest hospital emergency room right away.

What should I avoid while taking QUILLIVANT XR?

- QUILLIVANT XR should not be taken with MAOI medicines. Do not start taking QUILLIVANT XR if you stopped taking an MAOI in the last 14 days.
- Do not drink alcohol while taking QUILLIVANT XR. This may cause a faster release of your methylphenidate dose.

What are the possible side effects of QUILLIVANT XR?

QUILLIVANT XR may cause serious side effects, including:

- See “What is the most important information I should know about QUILLIVANT XR?” for information on reported heart and mental problems.

Other serious side effects include:

- Painful and prolonged erections (priapism) have occurred with methylphenidate. If you or your child develop priapism, seek medical help right away. Because priapism can cause long lasting damage, it should be checked by a health care provider right away.
- Circulation problems in fingers and toes (peripheral vasculopathy, including Raynaud’s phenomenon):
  Signs and symptoms may include:

- fingers or toes may feel numb, cool, painful

- fingers or toes may change color from pale, to blue, to red

Tell your healthcare provider if you or your child have numbness, pain, skin color change, or sensitivity to temperature in your fingers or toes, or if you or your child have any signs of unexplained wounds appearing on fingers or toes during treatment with QUILLIVANT XR.

- Slowing of growth (height and weight) in children. Children should have their height and weight checked often during treatment with QUILLIVANT XR. QUILLIVANT XR treatment may be stopped if your child is not gaining weight or height.

- Eye problems (increased pressure in the eye and glaucoma). Call your healthcare provider right away if you or your child develop changes in your vision or eye pain, swelling, or redness.

- New or worsening tics or worsening Tourette’s syndrome. Tell your healthcare provider if you or your child get any new or worsening tics or worsening Tourette’s syndrome during treatment with QUILLIVANT XR.

The most common side effects of QUILLIVANT XR include:

- decreased appetite
- trouble sleeping
- nausea
- vomiting
- indigestion
- stomach pain
- weight loss
- anxiety
- dizziness
- irritability
- mood swings
- fast heart beat
- increased blood pressure

These are not all the possible side effects of QUILLIVANT XR.

Call your doctor for medical advice about side effects. You may report side effects to FDA at 1-800-FDA-1088.

How should I store QUILLIVANT XR?

- Store QUILLIVANT XR at 59°F to 86°F (15°C to 30°C).
- Store QUILLIVANT XR in a safe place, like a locked cabinet.
- Dispose of remaining, unused, or expired QUILLIVANT XR by a medicine take-back program at a U.S. Drug Enforcement Administration (DEA) authorized collection site. If no take-back program or DEA authorized collector is available, mix QUILLIVANT XR with an undesirable, nontoxic substance such as dirt, cat litter, or used coffee grounds to make it less appealing to children and pets. Place the mixture in a container such as a sealed plastic bag and throw away QUILLIVANT XR in the household trash. Visit http://www.fda.gov/drugdisposal for additional information on disposal of unused medicines.
- Keep QUILLIVANT XR and all medicines out of the reach of children.

General information about the safe and effective use of QUILLIVANT XR

Medicines are sometimes prescribed for purposes other than those listed in a Medication Guide. Do not use QUILLIVANT XR for a condition for which it was not prescribed. Do not give QUILLIVANT XR to other people, even if they have the same condition. It may harm them.

You can ask your pharmacist or healthcare provider for information about QUILLIVANT XR that is written for healthcare professionals.

What are the ingredients in QUILLIVANT XR?

Active Ingredient: methylphenidate hydrochloride

Inactive Ingredients: sodium polystyrene sulfonate, povidone, triacetin, polyvinyl acetate, sucrose, anhydrous trisodium citrate, anhydrous citric acid, sodium benzoate, sucralose, poloxamer 188, corn starch, xanthan gum, talc, banana flavor, and silicon dioxide.

Distributed by:

Manufactured by:

Tris Pharma, Inc.

Monmouth Junction, NJ 08852

For more information, go to www.quillivantxr.com or call (732) 940-0358.

This product’s label may have been updated. For current full prescribing information, please visit www.trispharma.com.

This Medication Guide has been approved by the U.S. Food and Drug Administration. Revised:09/2025

PATIENT INFORMATION

Instructions for Use

QUILLIVANT XR® (\kwil-ə-vant\)
(methylphenidate hydrochloride)
for extended-release oral suspension CII

Read this Instructions for Use before using QUILLIVANT XR and each time you get a refill. There may be new information. This leaflet does not take the place of talking with the health care provider about your or your child’s medical condition or treatment.

Step 1. Remove the QUILLIVANT XR bottle and oral dosing dispenser from the box (See Figure A). If the oral dosing dispenser is missing or not provided, please contact your pharmacist for a replacement.
Step 2. Check and make sure that the QUILLIVANT XR bottle contains liquid medicine (See Figure B). If QUILLIVANT XR is still in powder form, do not use it. Return it to your pharmacist.

Step 3. Shake the bottle well (up and down) for at least 10 seconds before each use (See Figure C).

Step 4. Uncap the bottle and check that the bottle adapter has been fully inserted into the bottle (See Figure D).
Step 4 (continued). If bottle adapter (See Figure E) has not been inserted by the pharmacist into the bottle, insert adapter into the bottle as shown (See Figure E and Figure F).

After the bottle adapter has been fully inserted into the bottle (See Figure G), it should not be removed. If the bottle adapter has not been inserted and is missing from the box, contact your pharmacist.
The bottle adapter must be fully inserted and should be even with the mouth of the bottle and must remain in place to allow the child resistant cap to work the right way.

Step 5. Check the QUILLIVANT XR dose in milliliters (mL) as prescribed by your health care provider. Locate this number on the oral dosing dispenser (See Figure H).
Step 6. Insert tip of the oral dosing dispenser into the upright bottle and push the plunger all the way down (See Figure I).

Step 7. With the oral dosing dispenser in place, turn the bottle upside down. Pull the plunger to the number of mL you need (the amount of liquid medicine in Step 5 – See Figure J).
Step 7 (continued). Measure the number of mL of medicine from the white end of the plunger (See Figure K).
Step 8. Remove the oral dosing dispenser from the bottle adapter.
Step 9. Slowly squirt QUILLIVANT XR directly into your or your child’s mouth (See Figure L).

Step 10. Cap the bottle tightly. Store the bottle upright at 59°F to 86°F (15°C to 30°C) (See Figure M).
Figure M
Step 11. Clean the oral dosing dispenser after each use by placing in the dishwasher, or by rinsing with tap water (See Figure N).
Figure N

These Instructions for Use have been approved by the U.S. Food and Drug Administration. Revised: 06/2021

This product’s label may have been updated. For current full prescribing information, please visit www.trispharma.com.

Distributed by:

Manufactured by:
Tris Pharma, Inc.
Monmouth Junction, NJ 08852

LB8529

Rev. 01

06/2021

PRINCIPAL DISPLAY PANEL

NDC 24478-321-02
QUILLIVANT XR®
methylphenidate HCI
for extended-release oral suspension
300 mg/ 60 mL total volume
(When reconstituted with 53 mL of water)
25 mg/5 mL
(5 mg/mL) When reconstituted
Rx Only

PRINCIPAL DISPLAY PANEL

NDC 24478-322-04
QUILLIVANT XR®
methylphenidate HCI
for extended-release oral suspension
600 mg/ 120 mL total volume
(When reconstituted with 105 mL of water)
25 mg/5 mL
(5 mg/mL) When reconstituted
Rx Only

PRINCIPAL DISPLAY PANEL

NDC 24478-323-05
QUILLIVANT XR®
methylphenidate HCI
for extended-release oral suspension
750 mg/ 150 mL total volume
(When reconstituted with 131 mL of water)
25 mg/5 mL
(5 mg/mL) When reconstituted
Rx Only

PRINCIPAL DISPLAY PANEL

NDC 24478-324-06
QUILLIVANT XR®
methylphenidate HCI
for extended-release oral suspension
900 mg/ 180 mL total volume
(When reconstituted with 158 mL of water)
25 mg/5 mL
(5 mg/mL) When reconstituted
Rx Only